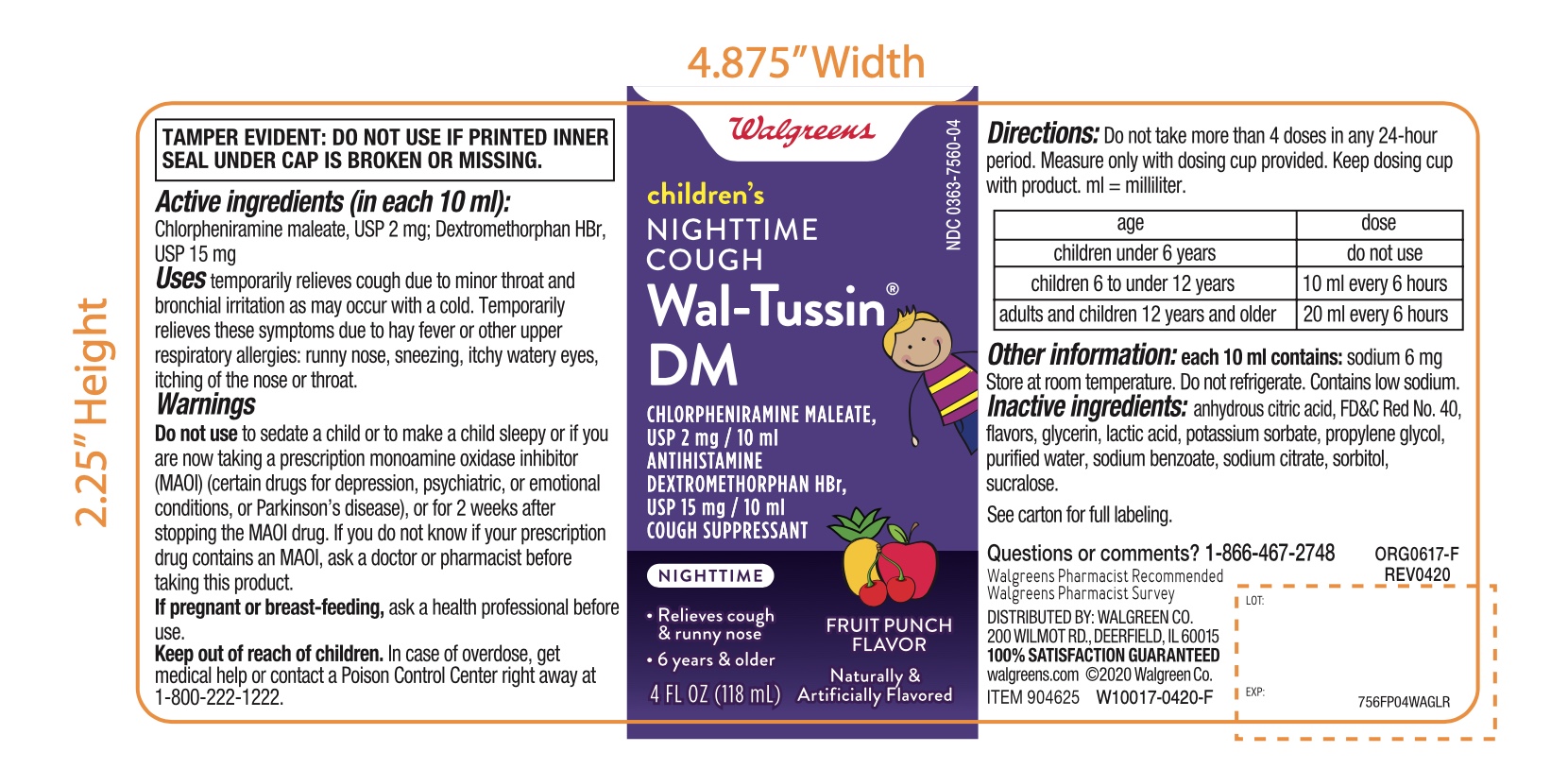 DRUG LABEL: Walgreens Childrens
NDC: 0363-7560 | Form: LIQUID
Manufacturer: WALGREENS CO.
Category: otc | Type: HUMAN OTC DRUG LABEL
Date: 20251201

ACTIVE INGREDIENTS: CHLORPHENIRAMINE MALEATE 2 mg/10 mL; DEXTROMETHORPHAN HYDROBROMIDE 15 mg/10 mL
INACTIVE INGREDIENTS: ANHYDROUS CITRIC ACID; FD&C RED NO. 40; GLYCERIN; LACTIC ACID, UNSPECIFIED FORM; POTASSIUM SORBATE; PROPYLENE GLYCOL; WATER; SODIUM BENZOATE; SODIUM CITRATE, UNSPECIFIED FORM; SORBITOL; SUCRALOSE

Walgreens Children’s Night-Time Cough & Chest Congestion

Active ingredients (in each 10 mL)

Chlorpheniramine maleate, USP 2 mg

Dextromethorphan HBr USP 15 mg

Purpose

Antihistamine

Cough suppressant

Uses

- temporarily relieves cough due to minor throat and bronchial irritation as may occur with a cold
- temporarily relieves these symptoms due to hay fever or other upper respiratory allergies:
- runny nose
- sneezing
- itching of the nose or throat
- itchy, watery eyes

Warnings

Do not us

- to sedate a child or to make a child sleepy
- if you are now taking a prescription monoamine oxidase inhibitor (MAOI) (certain drugs for depression, psychiatric or emotional conditions, or Parkinson's disease), or for 2 weeks after stopping the MAOI drug. If you do not know if your prescription drug contains an MAOI, ask a doctor or pharmacist before taking this product.

Ask a doctor before use if you have

- trouble urinating due to an enlarges prostate gland
- glaucoma
- a cough that occurs with too much phlegm (mucus)
- a breathing problem or chronic cough that lasts or as occurs with smoking, asthma, chronic bronchitis or emphysema

Ask a doctor or pharmacist before use if you are

taking sedatives or tranquilizers.

When using this product

- do not use more than directed.
- marked drowsiness may occur
- avoid alcoholic drinks
- alcohol, sedatives and tranquilizers may increase drowsiness
- be careful when driving a motor vehicle or operating machinery
- excitability may occur, especially in children

Stop use and ask a doctor if

- cough last more than 7 days, comes back or is accompanied by fever, rash, or persistent headache. These could be signs of a serious condition.

If pregnant or breast-feeding,

ask a health professional before use

Keep out of reach of children.

In case of overdose, get medical help or contact a Poison Control Center (1-800-222-1222) right away

Directions

- measure only with dosing cup provided.
- keep dosing cup with product
- mL= milliliter
- do not take more than 4 doses in any 24-hour period

age | dose
Children under 6 years | Do not use
Children 6 to under 12 years | 10 mL every 6 hours
Adults and children 12 years and older | 20 mL every 6 hours

Other information

- each 10 mL contains: sodium 3 mg
- store at room temperature. Do not refrigerate
- contain low sodium
- do not use if printed seal under cap is torn or missing

Inactive ingredients

anhydrous citric acid, FD&C Red # 40, flavor, potassium sorbate, potassium citrate, propylene glycol, purified water, sodium benzoate, sorbitol, sucralose

Questions or comments?

1-866-467-2748

Principal Display Panel

Compare to the Children's Robitussin®Nighttime Cough DM active ingredients††

NDC# 0363-7560-04

Children's

Nighttime Cough

Wal-Tussin®DM

CHLORPHENIRAMINE MALEATE, USP 2 mg/10 mL

ANTIHISTAMINE

DEXTROMETHORPHAN HBr, USP 15 mg/15 mL

COUGH SUPPRESSANT

NIGHTTIME

Relieves cough & runny nose

6 YEARS & OLDER

Fruit Punch Flavor

NATURALLY AND ARTIFICIALLY FLAVORED

Dosage cup included

2-4 FL OZ (118 mL) BOTTLES TOTAL – 8 FL OZ (236 mL)

Walgreens PHARMACIST RECOMMENDED†

Health expertise you rely on, quality you trust

†Walgreens Pharmacists Survey

*This product is not manufactured or distributed by Pfizer, owner of the registered trademarks Children’s Robitussin®

DISTRIBUTED BY: WALGREEN CO.

200 WILMOT RD., DEERFIELD, IL 60015

Walgreens

100% SATISFACTION GUARANTEED

Walgreens.com ©2020 Walgreen Co.